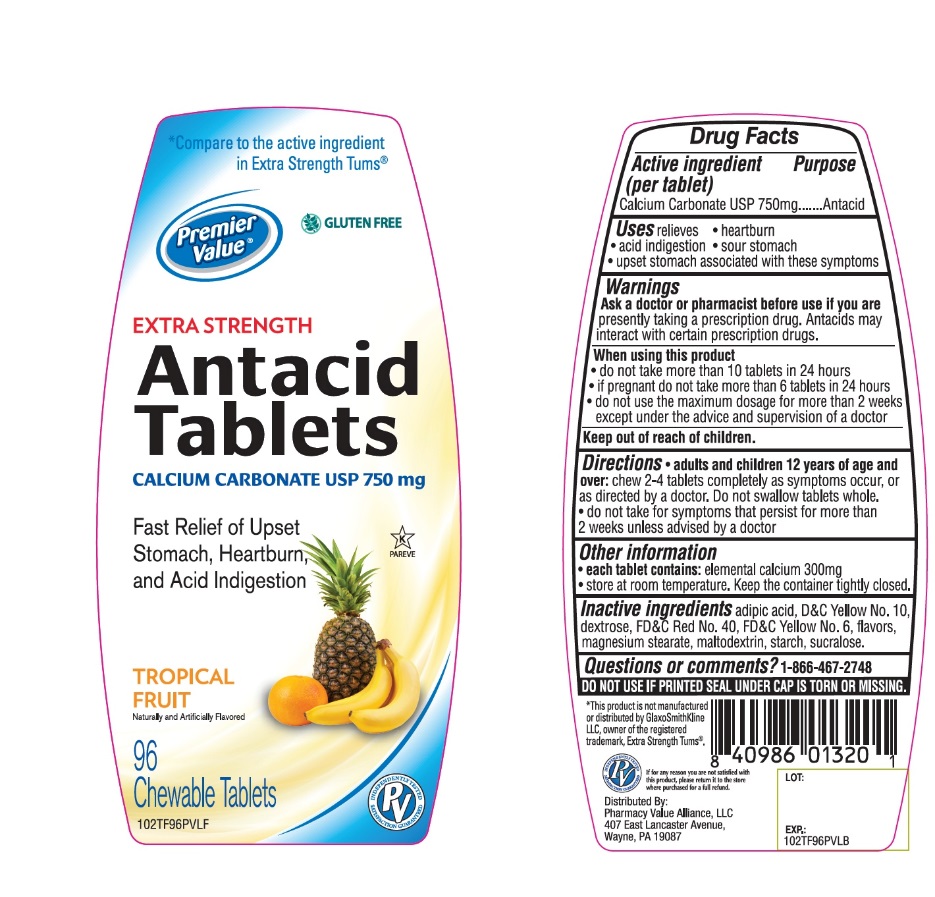 DRUG LABEL: Premier Value Chewable Antacid Extra Strength
NDC: 68016-668 | Form: TABLET, CHEWABLE
Manufacturer: Chain Drug Consortium
Category: otc | Type: HUMAN OTC DRUG LABEL
Date: 20241025

ACTIVE INGREDIENTS: CALCIUM CARBONATE 500 mg/1 1
INACTIVE INGREDIENTS: ADIPIC ACID; D&C YELLOW NO. 10; DEXTROSE, UNSPECIFIED FORM; FD&C RED NO. 40; FD&C YELLOW NO. 6; MAGNESIUM STEARATE; MALTODEXTRIN; STARCH, CORN; SUCRALOSE

Drug Facts

Active ingredient

Calcium carbonate USP 750mg

Purpose

Antacid

Uses

relieves:

• heartburn

• sour stomach

• acid indigestion

• upset stomach associated with these symptoms

Warnings

Ask a doctor or pharmacist before use if you are taking a prescription drug. Antacids may interact with certain prescription drugs.

When using this product

- do not take more than 10 tablets in 24 hours
- If pregnant do not take more than 6 tablets in 24 hours
- do not use the maximum dosage for more than 2 weeks except under the advice and supervision of a doctor.

Directions

• adults and children 12 years of age and over: chew 2-4 tablets as symptoms occur, or as directed by a doctor.

- Do not swallow tablets whole.
- Do not take for symptoms that persist for more than 2 weeks unless advised by a doctor.

Other Information

• each tablets contains: elemental calcium 300mg

• Keep the container tightly closed

• Store at room temperature.

Inactive ingredients

adipic acid, D&C Yellow No 10, dextrose, FD&C Red No 40, FD&C Yellow No. 6, flavors, magnesium stearate, maltodextrin, starch, sucralose.

Package/Label Principal Display Panel

Compare to the Active Ingredient in Tums*

Premier Value

Extra Strength

Antacid Tablets

Calcium Carbonate USP 750 mg

Fast Relief of Heartburn, Acid Indigestion & Upset Stomach

TROPICAL FRUIT

Naturally and Artificially Flavored

96 Chewable Tablets

Distributed by :

Pharmacy Value Alliance, LLC

407 East Lancaster Avenue,

Wayne, PA 19087

This product is not manufactured or distributed by GlaxoSmithKline, owner of the registered trademark, Extra Strength Tums®

Safety sealed: Do not use if printed seal under cap is torn or missing